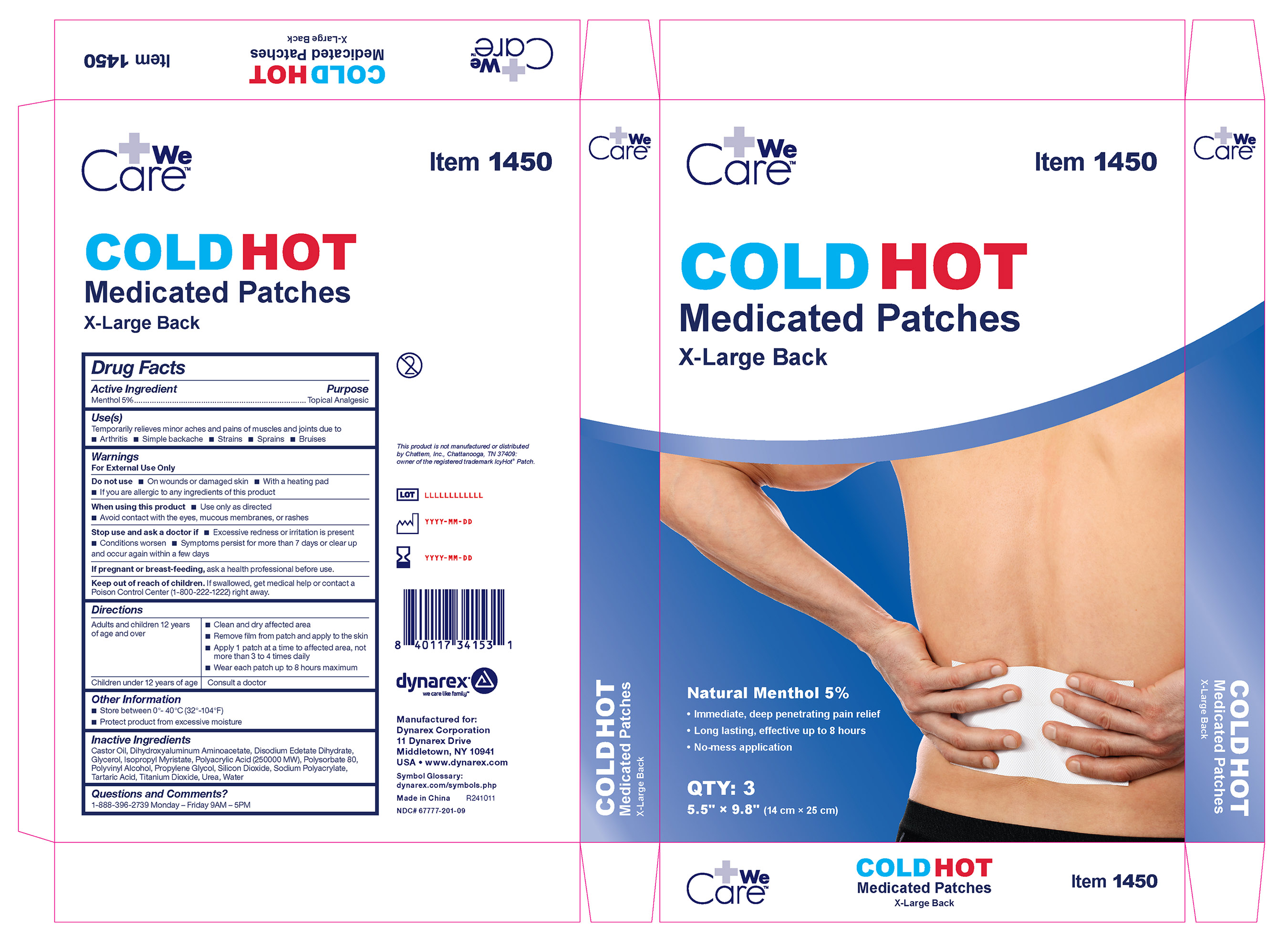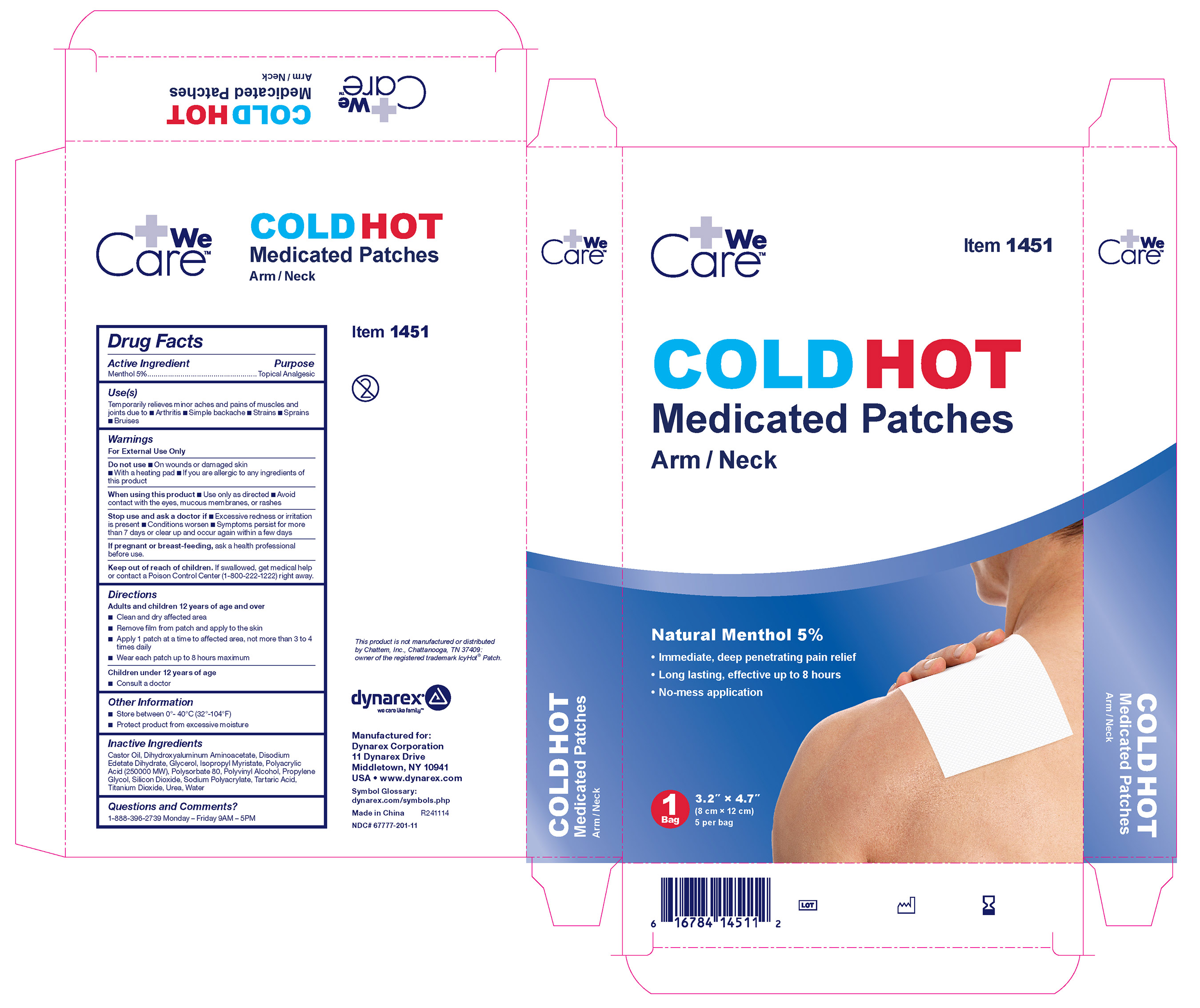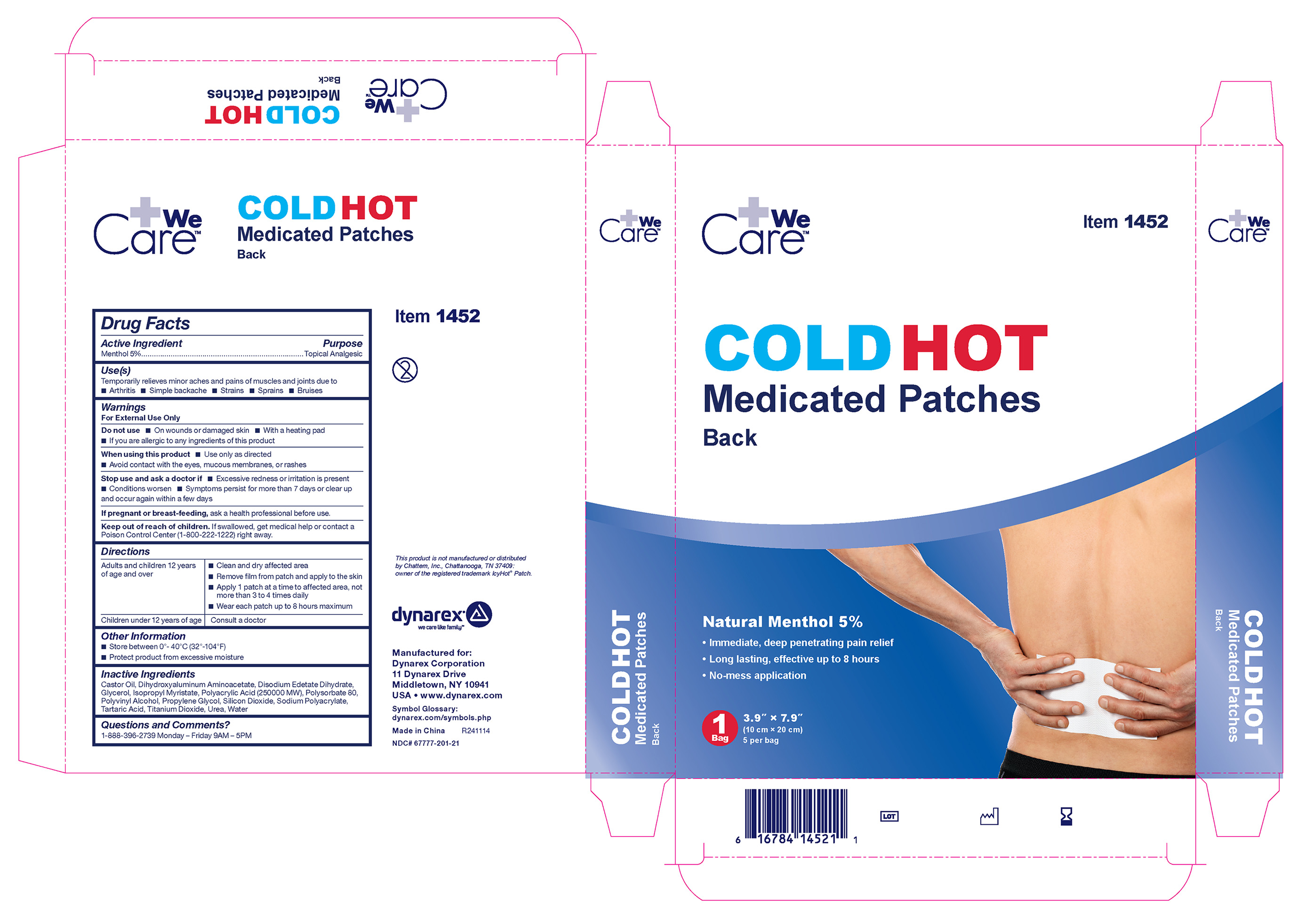 DRUG LABEL: Hot/Cold Medicated Patch
NDC: 67777-201 | Form: PATCH
Manufacturer: Dynarex
Category: otc | Type: HUMAN OTC DRUG LABEL
Date: 20250314

ACTIVE INGREDIENTS: MENTHOL 285 mg/5700 mg
INACTIVE INGREDIENTS: EDETATE DISODIUM; CASTOR OIL; POLYSORBATE 80; ISOPROPYL MYRISTATE; POLYVINYL ALCOHOL, UNSPECIFIED; SODIUM POLYACRYLATE (2500000 MW); TARTARIC ACID; TITANIUM DIOXIDE; WATER; GLYCERIN; POLYACRYLIC ACID (250000 MW); DIHYDROXYALUMINUM AMINOACETATE; PROPYLENE GLYCOL; UREA; SILICON DIOXIDE

1451 Cold/Hot Medictaed Patches Arm/Neck 67777-201-10
1452 Cold/Hot Medicated Patches Back 67777-201-20
1450 Cold/Hot Medicated Patches Back 67777-201-08

Active Ingredient

Menthol 5%

Purpose

Topical analgesic

Use

Temporarily relieves minor aches and pains of muscles and joints due to

- Arthritis
- Simple backache
- Strains
- Sprains
- Bruises

Warnings

For external use only

Do not use

- On wounds or damaged skin
- With a heating pad
- If you are allergic to any ingredients of this product

When using this product

- Use only as directed
- Avoid contact with the eyes, mucous membranes or rashes

Stop use and ask a doctor if

- Excessive redness or irritation is present
- Conditions worsen
- Symptoms persist for more than 7 days or clear up and occur again within a few days

If pregnant or breast-feeding

ask a health professional before use

Keep out of reach of children

If swallowed, get medical help or contact a Poison Control Center (1-800-222-1222) right away.

Directions

Adults and children 12 years of age and over

- Clean and dry affected area
- Remove film from patch and apply to the skin
- Apply 1 patch at a time to affected area,not more than 3 to 4 times daily
- Wear each patch up to 8 hours maximum

Children under 12 years of age, consult a doctor

Other information

- Avoid storing product in direct sunlight
- Protect product from excessive moisture

Inactive ingredients

Castor Oil, Dihydroxyaluminum Aminoacetate, Disodium Edetate Dihydrate, Glycerol, Isopropyl Myristate, Polyacrylic Acid (250000 MW), Polysorbate 80, Polyvinyl Alcohol, Propylene Glycol, Silicon Dioxide, Sodium Polyacrylate, Tartaric Acid, Titanium Dioxide, Urea, Water

Questions and Comments?

1-888-396-2739 Monday - Friday 9AM - 5PM EST

Label

Cold Hot Medicated Patch 1450

Label

Cold Hot Medicated Patch 1451

Label

Cold Hot Medicated Patch 1452